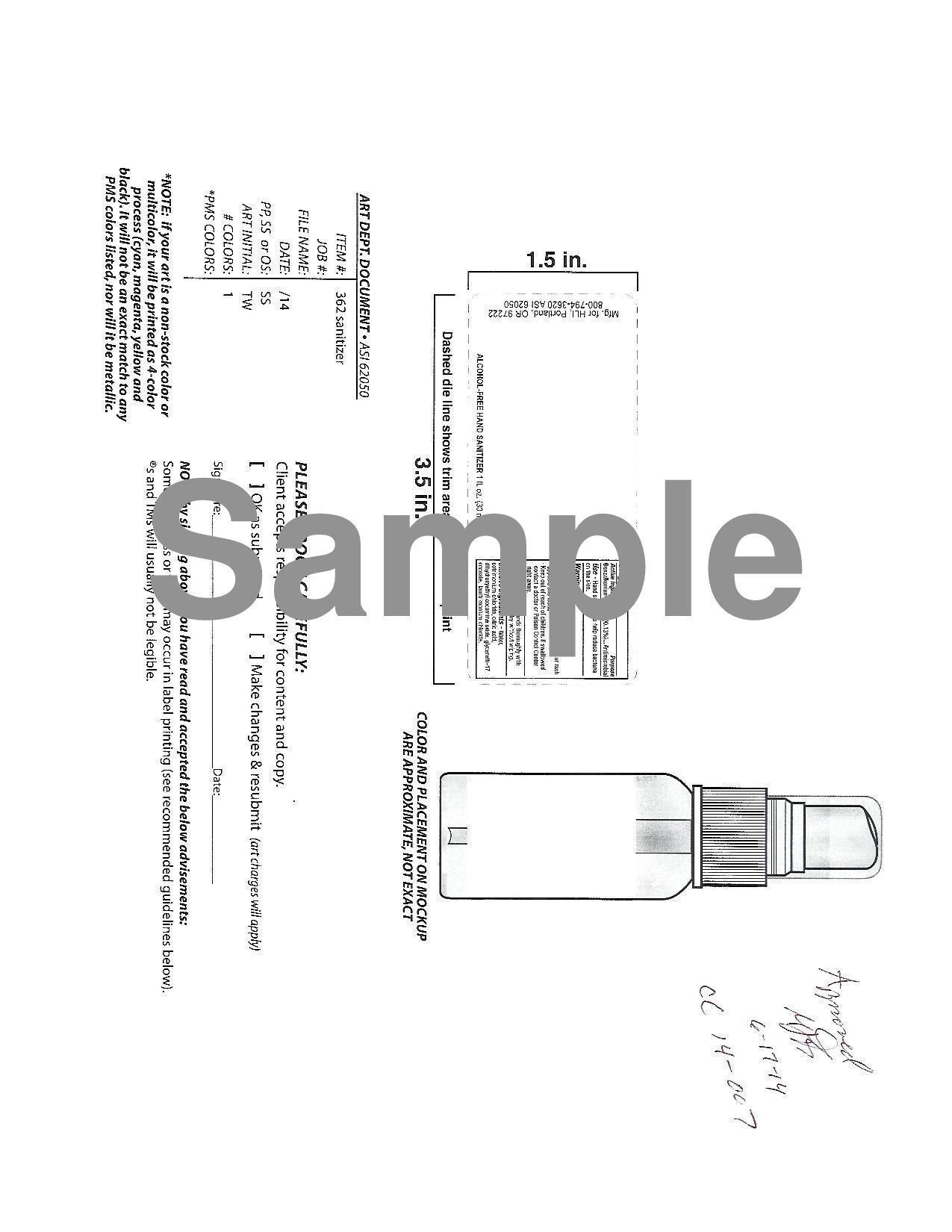 DRUG LABEL: Hand Sanitizer
                
NDC: 19392-120 | Form: LIQUID
Manufacturer: Humphreyline
Category: otc | Type: HUMAN OTC DRUG LABEL
Date: 20140702

ACTIVE INGREDIENTS: BENZALKONIUM CHLORIDE 1.3 g/1000 g
INACTIVE INGREDIENTS: WATER; CETRIMONIUM CHLORIDE; CITRIC ACID MONOHYDRATE; DIHYDROXYETHYL COCAMINE OXIDE; GLYCERETH-17 COCOATE; LAURTRIMONIUM CHLORIDE

Drug Facts

ACTIVE INGREDIENT

Benzalkonium chloride 0.13%

PURPOSE

Antimicrobial

Keep out of reach of children

INDICATIONS AND USAGE

Hand sanitizer to help reduce bacteria on the skin

WARNINGS

For external use only

Do not use in or near the eyes

Stop use and ask a doctor if irritation or rash appears and lasts

Keep out of reach of children. If swallowed contact a doctor or Poison Control Center right away

DOSAGE AND ADMINISTRATION

Wet hands thoroughly with product and allow to dry without wiping

INACTIVE INGREDIENT

Water, cetrimonium chloride, citric acid, dihydroxyethyl cocamine oxide, glycereth-17 cocoate, laurtrimonium chloride

nonalcohol